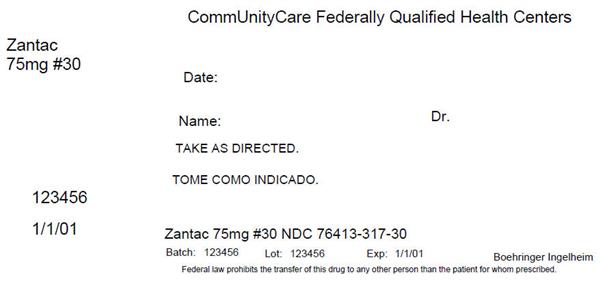 DRUG LABEL: Zantac
NDC: 76413-317 | Form: TABLET, COATED
Manufacturer: Central Texas Community Health Centers
Category: otc | Type: HUMAN OTC DRUG LABEL
Date: 20180426

ACTIVE INGREDIENTS: RANITIDINE HYDROCHLORIDE 75 mg/1 1
INACTIVE INGREDIENTS: HYPROMELLOSE, UNSPECIFIED; magnesium stearate; MICROCRYSTALLINE CELLULOSE; ferric oxide red; titanium dioxide; triacetin

Zantac 75® Drug Facts

Drug Facts

Active ingredient (in each tablet) | Purpose
Ranitidine 75 mg (as ranitidine hydrochloride 84 mg) . . . . . . . . . . . . . . . . . . . . . . . . . . . . . . . . . . . . . . . . . . . . . . . . . . | Acid reducer

Uses

- relieves heartburn associated with acid indigestion and sour stomach
- prevents heartburn associated with acid indigestion and sour stomach brought on by eating or drinking certain foods and beverages

Warnings

Allergy alert: Do not use if you are allergic to ranitidine or other acid reducers

Do not use

- if you have trouble or pain swallowing food, vomiting with blood, or bloody or black stools. These may be signs of a serious condition. See your doctor.
- with other acid reducers

Ask a doctor before use if you have

- had heartburn over 3 months. This may be a sign of a more serious condition.
- heartburn with lightheadedness, sweating or dizziness
- chest pain or shoulder pain with shortness of breath; sweating; pain spreading to arms, neck or shoulders; or lightheadedness
- frequent chest pain
- frequent wheezing, particularly with heartburn
- unexplained weight loss
- nausea or vomiting
- stomach pain

Stop use and ask a doctor if

- your heartburn continues or worsens
- you need to take this product for more than 14 days

If pregnant or breast-feeding, ask a health professional before use.

Keep out of reach of children. In case of overdose, get medical help or contact a Poison Control Center right away.

Directions

- adults and children 12 years and over:
  - to relieve symptoms, swallow 1 tablet with a glass of water
  - to prevent symptoms, swallow 1 tablet with a glass of water 30 to 60 minutes before eating food or drinking beverages that cause heartburn
  - can be used up to twice daily (do not take more than 2 tablets in 24 hours)
  - do not chew tablet
- children under 12 years: ask a doctor

Other information

- do not use if printed foil under bottle cap is open or torn (bottles)
- do not use if individual blister unit is open or torn (blisters)
- do not use if individual foil packet is open or torn (pouch)
- store at 20-25ºC (68-77ºF)
- avoid excessive heat or humidity
- this product is sodium and sugar free

Inactive ingredients

hypromellose, magnesium stearate, microcrystalline cellulose, iron oxide, titanium dioxide, triacetin

Questions?

call 1-888-285-9159 (English/Spanish) M – F, 8:30 – 5 EST, or visit www.zantacotc.com

Read the directions, consumer information leaflet and warnings before use. Keep the carton. It contains important information.

Distributed by: Boehringer Ingelheim (BI) Consumer Health Care Products
Division of BI Pharmaceuticals, Inc., Ridgefield, CT 06877
© 2016, BI Pharmaceuticals, Inc. All rights reserved.
Product of Spain. Manufactured in Mexico.

HOW SUPPLIED

Product: 76413-317

NDC: 76413-317-30 10 TABLET, COATED in a BLISTER PACK / 3 in a CARTON